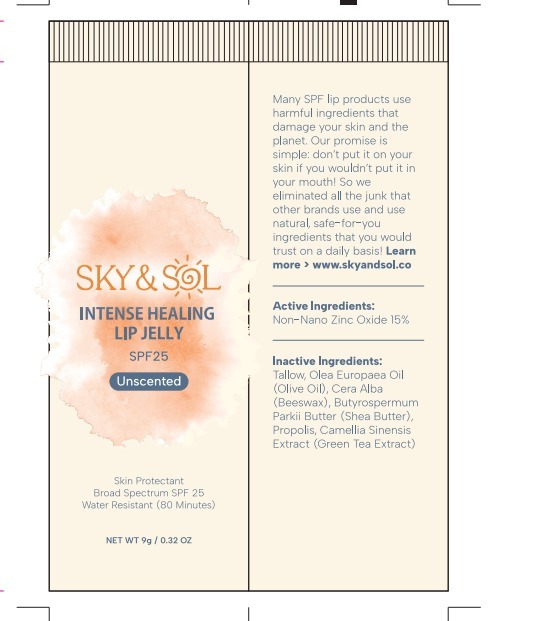 DRUG LABEL: Sky and Sol Intense Healing Lip Jelly
NDC: 84632-0025 | Form: OINTMENT
Manufacturer: Delta Ecommerce LLC
Category: otc | Type: HUMAN OTC DRUG LABEL
Date: 20250211

ACTIVE INGREDIENTS: ZINC OXIDE 25 g/100 g
INACTIVE INGREDIENTS: BEESWAX; SHEA BUTTER; PROPOLIS CERA; GREEN TEA LEAF; TALLOW; OLIVE OIL

INACTIVE INGREDIENT

Tallow, Olea Europaea (Olive) Fruit Oil, Cera Alba (Beeswax),
Butyrospermum Parkii (Shea) Butter, Propolis Cera (Propolis),
Camellia Sinensis (Green Tea) Leaf Extract

PURPOSE

SUNSCREEN

KEEP OUT OF REACH OF CHILDREN

If product is swallowed,
get medical help or contact a Poison Control Center
right away.

WARNINGS

For external use only.
Do not use on damaged or broken skin.
When using this product keep out of eyes. Rinse
with water to remove.

DOSAGE AND ADMINISTRATION

shake well before use
apply liberally 15 minutes before sun exposure
reapply: • after 80 minutes of swimming or sweating
• immediately after towel drying • at least every 2 hours
children after 6 months of age: ask a doctor

INDICATIONS AND USAGE

Indications & Usage: helps prevent sunburn; if used as directed with other sun protection measures (see Directions), decreases the risk of skin cancer and early skin aging caused by the sun.